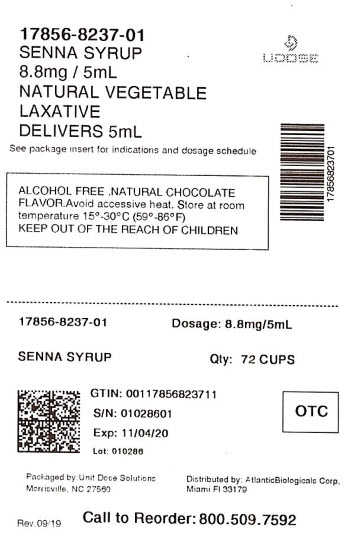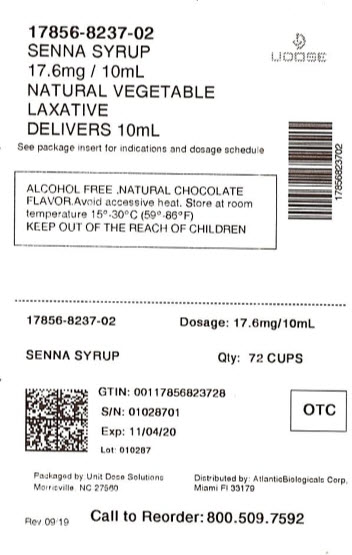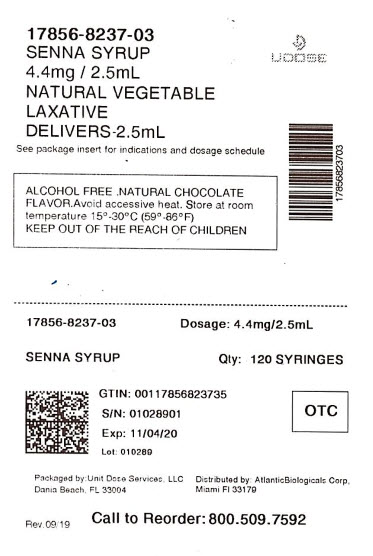 DRUG LABEL: SENNA
NDC: 17856-8237 | Form: SYRUP
Manufacturer: ATLANTIC BIOLOGICALS CORP.
Category: otc | Type: HUMAN OTC DRUG LABEL
Date: 20250731

ACTIVE INGREDIENTS: SENNOSIDES A AND B 417.12 mg/237 mL
INACTIVE INGREDIENTS: METHYLPARABEN; PROPYLENE GLYCOL; PROPYLPARABEN; WATER; SUCROSE

SENNA SYRUP
Natural Vegitable Lexative

Active Ingredient

Active ingredient (in each 5 ml) purpose
Sennosides 8.8 mg …………………………................Laxative

Uses

relieves occasional constipation (irregularity)
generally causes bowel movement in 6 to 12 hours

Directions

shake well before use
take preferably at bedtime or as directed by a doctor

DOSAGE AND ADMINISTRATION

Age Starting Dose Maximum Dose
adults and children 12 years 2 - 3 teaspoonfuls 3 teaspoonfuls twice a day
and older once a day

6 years to under 12 years of age 1 - 1½ teaspoonfuls once a day 1½ teaspoonfuls twice a day

2 to under 6 years of age ½ - ¾ teaspoon once a day ¾ teaspoon once a day

under 2 years of age consult a doctor consult a doctor

Warnings

Do Not Use • laxative products for longer than 1 week
unless directed by a doctor
Ask a doctor or pharmacist before use if you have
• stomach pain • nausea • vomiting
• notice a sudden change in bowel movement that continues
over a period of 2 weeks
Stop use and ask a doctor if
you have rectal bleeding or failure to have a bowel movement
after use of laxative. These may indicate a serious condition
If pregnant or breast-feeding, ask a health
professional before use

Other Information

- Avoid accessive heat. Store at room temperature 15°-30°C (59°-86°F)

Inactive Ingredients

Mythylparaben, Propylene Glycol, Propylparaben, Purified Water, Sucrose

KEEP OUT OF REACH OF CHILDREN SECTION

In case of accidental overdose, get medical help or contact a Poison Control Center immediately

Questions?

To Report Adverse Drug Event Call 1(877) 225-6999

DISTRIBUTED BY:

ATLANTIC BIOLOGICALS CORP.

20101 N.E 16TH PLACE

MIAMI, FL 33179